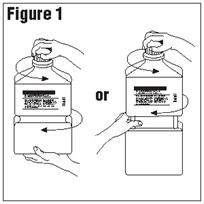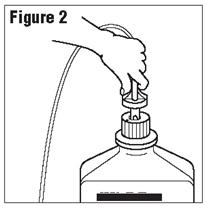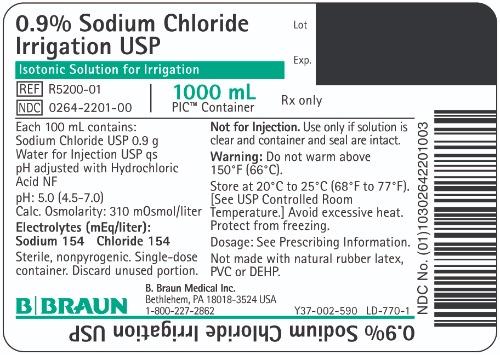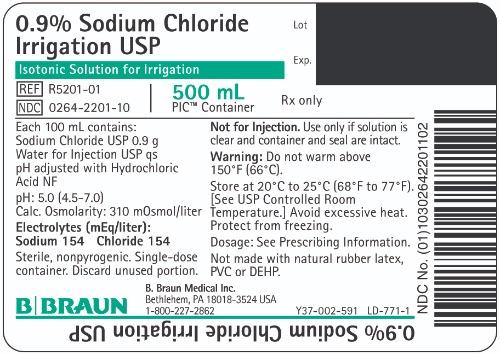 DRUG LABEL: Sodium Chloride
NDC: 0264-2201 | Form: IRRIGANT
Manufacturer: B. Braun Medical Inc.
Category: prescription | Type: HUMAN PRESCRIPTION DRUG LABEL
Date: 20230907

ACTIVE INGREDIENTS: SODIUM CHLORIDE 0.9 g/100 mL
INACTIVE INGREDIENTS: WATER; HYDROCHLORIC ACID

0.9% Sodium Chloride Irrigation USP

Package Insert

PIC™ (Plastic Irrigation Container)

0.9% Sodium Chloride Irrigation USP

Isotonic Solution for Irrigation.

For Irrigation Only.

Not for Injection.

Rx only

DESCRIPTION

Each 100 mL contains:
Sodium Chloride USP 0.9 g; Water for Injection USP qs

pH adjusted with Hydrochloric Acid NF
pH: 5.0 (4.5–7.0) Calculated Osmolarity: 310 mOsmol/liter

Concentration of Electrolytes (mEq/liter): Sodium 154; Chloride 154

0.9% Sodium Chloride Irrigation USP is sterile, nonpyrogenic, isotonic and contains no bacteriostatic or antimicrobial agents.

The formula of the active ingredient is:

Ingredient | Molecular Formula | Molecular Weight
Sodium Chloride USP | NaCl | 58.44

The plastic container is a copolymer of ethylene and propylene formulated and developed for parenteral drugs. The copolymer contains no plasticizers and exhibits virtually no leachability. The plastic container is also virtually impermeable to vapor transmission and, therefore, requires no overwrap to maintain the proper drug concentration. The safety of the plastic container has been confirmed by biological evaluation procedures. The material passes Class Vl testing as specified in the U.S. Pharmacopeia for Biological Tests — Plastic Containers. These tests have shown that the container is nontoxic and biologically inert.

Not made with natural rubber latex, PVC or DEHP.

CLINICAL PHARMACOLOGY

0.9% Sodium Chloride Irrigation USP is utilized for a variety of clinical indications such as sterile irrigation of body cavities, tissues or wounds, indwelling urethral catheters, surgical drainage tubes, and for washing, rinsing or soaking surgical dressings, instruments and laboratory specimens. It also serves as a diluent or vehicle for drugs used for irrigation or other pharmaceutical preparations.

0.9% Sodium Chloride Irrigation USP provides an isotonic saline irrigation identical in composition with 0.9% Sodium Chloride Injection USP (normal saline).

Physiological irrigation solutions are considered generally compatible with living tissues and organs.

Sodium, the major cation of the extracellular fluid, functions primarily in the control of water distribution, fluid balance, and osmotic pressure of body fluids. Sodium is also associated with chloride and bicarbonate in the regulation of the acid-base equilibrium of body fluid.

Chloride, the major extracellular anion, closely follows the metabolism of sodium, and changes in the acid-base balance of the body are reflected by changes in the chloride concentration.

INDICATIONS AND USAGE

0.9% Sodium Chloride Irrigation USP is indicated for all general irrigation, washing, rinsing and dilution purposes which permit use of a sterile, nonpyrogenic electrolyte solution.

CONTRAINDICATIONS

0.9% Sodium Chloride Irrigation USP is not for injection by usual parenteral routes.

An electrolyte solution should not be used for irrigation during electrosurgical procedures.

WARNINGS

FOR IRRIGATION ONLY. NOT FOR INJECTION.

Irrigating fluids have been demonstrated to enter the systemic circulation in relatively large volumes; thus, irrigation solutions must be regarded as systemic drugs. Absorption of large amounts can cause fluid and/or solute overload resulting in dilution of serum electrolyte concentrations, overhydration, congested states or pulmonary edema.

The risk of dilutional states is inversely proportional to the electrolyte concentrations of the administered parenteral solutions. The risk of solute overload causing congested states with peripheral and pulmonary edema is directly proportional to the electrolyte concentration.

Do not warm above 150°F (66°C).

After opening container, its contents should be used promptly to minimize the possibility of bacterial growth or pyrogen formation.

Discard unused portion of irrigating solution since it contains no preservatives.

PRECAUTIONS

General

Use aseptic technique when preparing and administering sterile irrigation solutions.

Use only if solution is clear and container and seal are intact.

Do not use for irrigation that may result in absorption of large amounts of fluid into the blood.

Caution should be observed when the solution is used for continuous irrigation or allowed to “dwell” inside body cavities because of possible absorption into the blood stream and the production of circulatory overload.

When used for irrigation via appropriate irrigation equipment, the administration set should be attached promptly. Unused portions should be discarded and a fresh container of appropriate size used for the start up of each cycle or repeat procedure. For repeated irrigations of urethral catheters, a separate container should be used for each patient.

Laboratory Tests

Clinical evaluation and periodic laboratory determinations are necessary to monitor changes in fluid balance, electrolyte concentrations, and acid-base balance after prolonged irrigation, when fluid absorption is suspected, or whenever the condition of the patient warrants such evaluation.

Drug Interactions

Some additives may be incompatible. Consult with pharmacist. When introducing additives, use aseptic technique. Mix thoroughly. Do not store.

Carcinogenesis, Mutagenesis, Impairment of Fertility

Studies with 0.9% Sodium Chloride Irrigation USP have not been performed to evaluate carcinogenic potential, mutagenic potential, or effects on fertility.

Pregnancy

Teratogenic Effects

Animal reproduction studies have not been conducted with 0.9% Sodium Chloride Irrigation USP. It is also not known whether 0.9% Sodium Chloride Irrigation USP can cause fetal harm when administered to a pregnant woman or can affect reproduction capacity. 0.9% Sodium Chloride Irrigation USP should be given to a pregnant woman only if clearly needed.

Labor and Delivery

Safety and effectiveness of 0.9% Sodium Chloride Irrigation USP during labor and delivery have not been established. Caution should be exercised, and the fluid balance, glucose and electrolyte concentrations, and acid-base balance, of both mother and fetus should be evaluated periodically or whenever warranted by the condition of the patient or fetus.

Nursing Mothers

It is not known whether this drug is excreted in human milk. Because many drugs are excreted in human milk, caution should be exercised when 0.9% Sodium Chloride Irrigation USP is administered to a nursing woman.

Pediatric Use

The safety and effectiveness of 0.9% Sodium Chloride Irrigation USP in pediatric patients have not been established. Its limited use in pediatric patients has been inadequate to fully define proper dosage and limitations for use.

Geriatric Use

Clinical studies of 0.9% Sodium Chloride Irrigation USP did not include a sufficient number of patients age 65 years and over to determine whether they respond differently from younger subjects. In general, dose selection for an elderly patient should be cautious, usually starting at the low end of the dosing range, reflecting the greater frequency of decreased hepatic, renal, or cardiac function, and of concomitant disease or other drug therapy.

This drug is known to be substantially excreted by the kidney, and the risk of toxic reactions to this drug may be greater in patients with impaired renal function. Because elderly patients are more likely to have decreased renal function, care should be taken in dose selection, and it may be useful to monitor renal function. Frequent laboratory determinations and clinical evaluations are recommended to monitor changes in blood glucose, electrolyte concentrations, and renal function.

ADVERSE REACTIONS

Possible adverse effects arising from the irrigation of body cavities, tissues, or indwelling catheters and tubes can be minimized when proper procedures are followed. Displaced catheters or drainage tubes can lead to irrigation or infiltration of unintended structures or cavities. Excessive volume or pressure during irrigation of closed cavities may cause undue distension or disruption of tissues. Accidental contamination from careless technique may transmit infection.

If an adverse reaction does occur, discontinue administration of the irrigant, evaluate the patient, institute appropriate therapeutic countermeasures, and save the remainder of the fluid for examination if deemed necessary.

OVERDOSAGE

In the event of overhydration or solute overload, reevaluate the patient’s condition, and institute appropriate corrective treatment. Intravascular volume overload may respond to hemodialysis. See WARNINGS, PRECAUTIONS, and ADVERSE REACTIONS.

DOSAGE AND ADMINISTRATION

As required for irrigation.

When used as a diluent, or vehicle for other drugs, the drug manufacturer’s recommendations should be followed.

Some additives may be incompatible. Consult with pharmacist. When introducing additives, use aseptic techniques. Mix thoroughly. Do not store.

Solutions should be inspected visually for particulate matter and discoloration prior to administration, whenever solution and container permits.

HOW SUPPLIED

0.9% Sodium Chloride Irrigation USP is supplied sterile and nonpyrogenic in PIC™ (Plastic Irrigation Container). The 1000 mL and 500 mL containers are packaged 16 per case.

NDC | Cat. No. | Size
0.9% Sodium Chloride Irrigation USP
0264-2201-00 | R5200-01 | 1000 mL
0264-2201-10 | R5201-01 | 500 mL

Exposure of pharmaceutical products to heat should be minimized. Avoid excessive heat. Protect from freezing. Store at 20°C to 25°C (68°F to 77°F); excursions permitted between 15°C to 30°C (59°F to 86°F). [See USP Controlled Room Temperature.] However, brief exposure up to 40°C does not adversely affect the product.

Do not warm above 150°F (66°C).

Revised: June 2023

PIC is a trademark of B. Braun Medical Inc.

Directions for Use of PIC™ (Plastic Irrigation Container)

Not for injection.

Aseptic technique is required.

1. Caution – Before use, perform the following checks:
  (a) Read the label. Ensure solution is the one ordered and is within the expiration date.
  (b) Invert container and inspect the solution in good light for cloudiness, haze, or particulate matter; check the
  container for leakage or damage. Any container which is suspect should not be used.
  Use only if solution is clear and container and seal are intact.
  Single-dose container. Discard unused portion.
2. Outer Closure Removal – Grasp the container with one hand and turn the breakaway ring counterclockwise with the other hand until slight resistance is felt. Then, twisting the container in the opposite direction, turn the breakaway ring sharply until the entire outer cap is loose and can be lifted off. (Figure 1)
3. Connect the administration set through the sterile set port according to set instructions (Figure 2) or remove screw cap and pour.
4. Do not warm above 150°F (66°C) to assure minimal bottle distortion. Keep bottles upright.

B. Braun Medical Inc.
Bethlehem, PA 18018-3524 USA
1-800-227-2862
Y36-003-074 LD-769-1

PRINCIPAL DISPLAY PANEL - 1000 mL Container

0.9% Sodium Chloride Irrigation USP

Isotonic Solution for Irrigation

REF R5200-01
NDC 0264-2201-00

1000 mL
PIC™ Container

Rx only

Lot
Exp.

Each 100 mL contains:
Sodium Chloride USP 0.9 g
Water for Injection USP qs
pH adjusted with Hydrochloric
Acid NF

pH: 5.0 (4.5-7.0)
Calc. Osmolarity: 310 mOsmol/liter

Electrolytes (mEq/liter):
Sodium 154 Chloride 154

Sterile, nonpyrogenic. Single-dose container. Discard unused portion.

Not for Injection. Use only if solution is clear and container and seal are intact.

Warning: Do not warm above 150°F (66°C).

Store at 20°C to 25°C (68°F to 77°F). [See USP Controlled Room Temperature.] Avoid excessive heat. Protect from freezing.

Dosage: See Prescribing Information.

Not made with natural rubber latex, PVC or DEHP.

B. Braun Medical Inc.
Bethlehem, PA 18018-3524 USA
1-800-227-2862

Y37-002-590 LD-770-1

0.9% Sodium Chloride Irrigation USP

PRINCIPAL DISPLAY PANEL - 500 mL Container

0.9% Sodium Chloride Irrigation USP

Isotonic Solution for Irrigation

REF R5201-01
NDC 0264-2201-10

500 mL
PIC™ Container

Rx only

Lot
Exp.

Each 100 mL contains:
Sodium Chloride USP 0.9 g
Water for Injection USP qs
pH adjusted with Hydrochloric
Acid NF

pH: 5.0 (4.5-7.0)
Calc. Osmolarity: 310 mOsmol/liter

Electrolytes (mEq/liter):
Sodium 154 Chloride 154

Sterile, nonpyrogenic. Single-dose container. Discard unused portion.

Not for Injection. Use only if solution is clear and container and seal are intact.

Warning: Do not warm above 150°F (66°C).

Store at 20°C to 25°C (68°F to 77°F). [See USP Controlled Room Temperature.] Avoid excessive heat. Protect from freezing.

Dosage: See Prescribing Information.

Not made with natural rubber latex, PVC or DEHP.

B. Braun Medical Inc.
Bethlehem, PA 18018-3524 USA
1-800-227-2862

Y37-002-591 LD-771-1

0.9% Sodium Chloride Irrigation USP